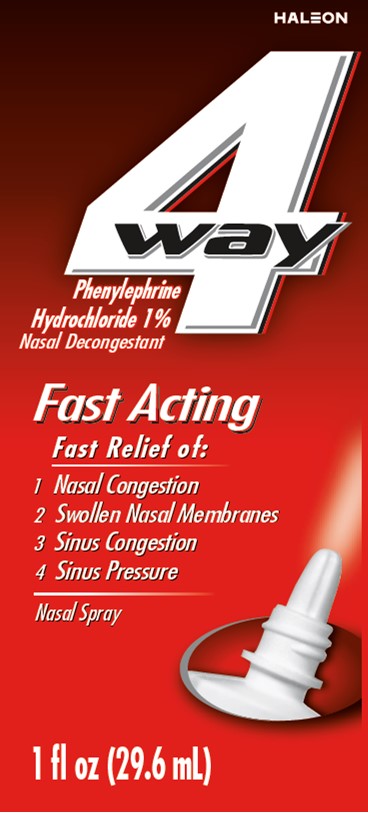 DRUG LABEL: 4 Way

NDC: 0067-2086 | Form: SPRAY
Manufacturer: Haleon US Holdings LLC
Category: otc | Type: HUMAN OTC DRUG LABEL
Date: 20251112

ACTIVE INGREDIENTS: PHENYLEPHRINE HYDROCHLORIDE 10 mg/1 mL
INACTIVE INGREDIENTS: BENZALKONIUM CHLORIDE; BENZYL ALCOHOL; BORIC ACID; WATER; SODIUM BORATE

Drug Facts

Active ingredient

Phenylephrine hydrochloride 1%

Purpose

Nasal Decongestant

Uses

- temporarily relieves nasal congestion due to:
  - common cold
  - hay fever
  - upper respiratory allergies

Warnings

Ask a doctor before use if you have

- heart disease
- diabetes
- thyroid disease
- high blood pressure
- trouble urinating due to an enlarged prostate gland

When using this product

- do not use more than directed
- do not use for more than 3 days. Frequent or prolonged use may cause nasal congestion to come back or get worse.
- use only as directed
- temporary discomfort such as burning, stinging, sneezing or an increase in nasal discharge may occur
- use of this container by more than one person may spread infection

Keep out of reach of children.

If swallowed, get medical help or contact a Poison Control Center right away. (1-800-222-1222)

Directions

- adults and children 12 years and over: 2 or 3 sprays in each nostril not more often than every 4 hours
- children under 12 years: ask a doctor
- Use instructions: with head in a normal, upright position, put atomizer tip into nostril. Squeeze bottle with firm, quick pressure while inhaling. Wipe nozzle clean after each use.

Other information

- store at 20°-25°C (68°-77°F)

Inactive ingredients

benzalkonium chloride solution, benzyl alcohol, boric acid, purified water, sodium borate

Questions or comments?

1-855-297-3031

Additional Information

READ ALL PRODUCT INFORMATION BEFORE USING.

KEEP CARTON FOR IMPORTANT INFORMATION.

DO NOT USE IF PRINTED NECKBAND IS BROKEN OR MISSING

Principal Display

4 way
Phenylephrine Hydrochloride 1%

Nasal Decongestant

Fast Acting

Fast Relief of:

1. Nasal Congestion
2. Swollen Nasal Membranes
3. Sinus Congestion
4. Sinus Pressure

Nasal Spray

1 fl oz (29.6 mL)